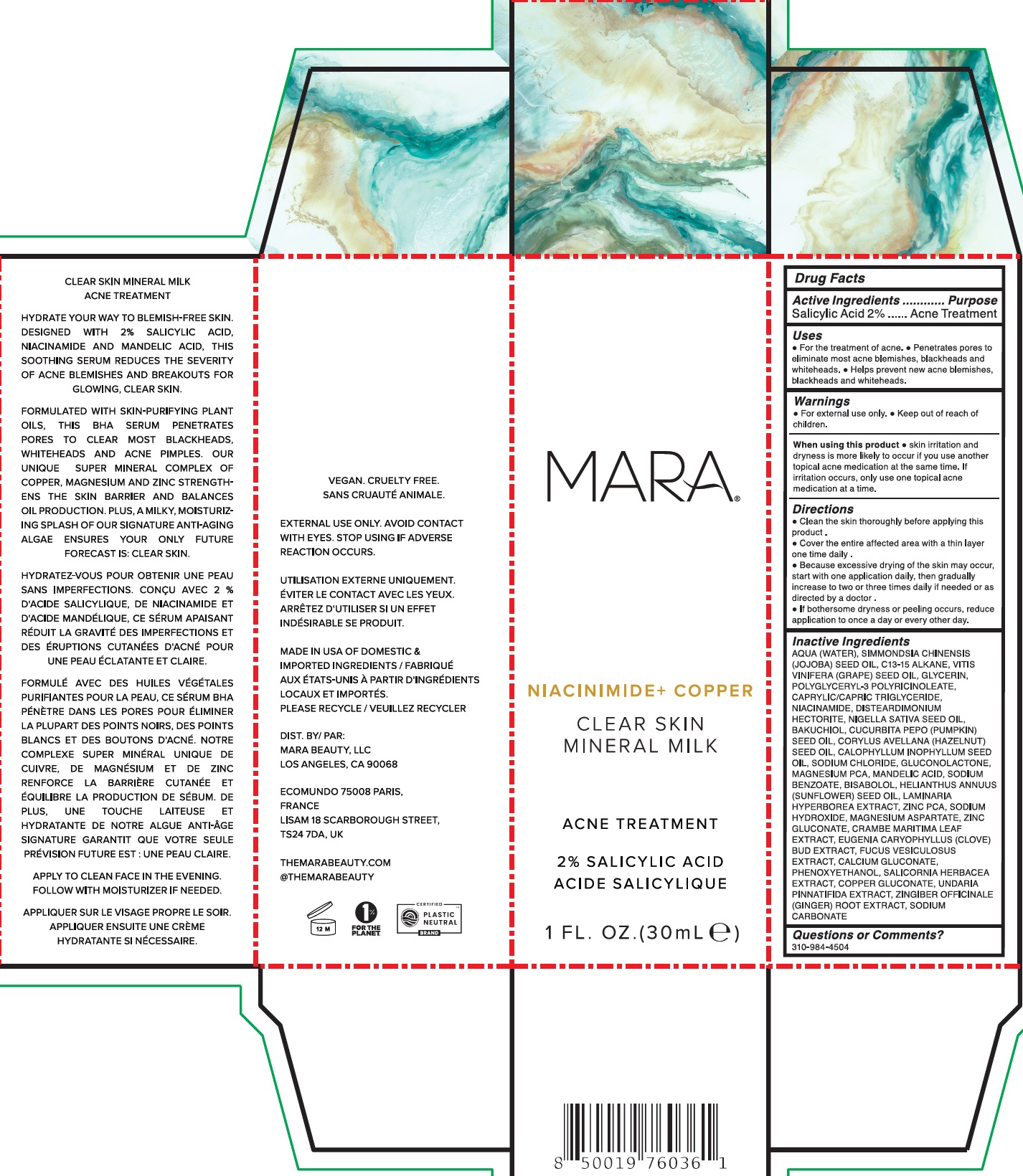 DRUG LABEL: Mara Clear Skin Mineral Milk Acne Treatment
NDC: 81461-002 | Form: LIQUID
Manufacturer: Mara Beauty LLC
Category: otc | Type: HUMAN OTC DRUG LABEL
Date: 20240613

ACTIVE INGREDIENTS: SALICYLIC ACID 20 mg/1 mL
INACTIVE INGREDIENTS: WATER; JOJOBA OIL; C13-15 ALKANE; GRAPE SEED OIL; GLYCERIN; MEDIUM-CHAIN TRIGLYCERIDES; NIACINAMIDE; DISTEARDIMONIUM HECTORITE; NIGELLA SATIVA SEED OIL; BAKUCHIOL; PUMPKIN SEED OIL; EUROPEAN HAZELNUT OIL; TAMANU OIL; SODIUM CHLORIDE; GLUCONOLACTONE; MAGNESIUM PIDOLATE; MANDELIC ACID; SODIUM BENZOATE; LEVOMENOL; SUNFLOWER OIL; LAMINARIA HYPERBOREA; ZINC PIDOLATE; SODIUM HYDROXIDE; MAGNESIUM ASPARTATE; ZINC GLUCONATE; CRAMBE MARITIMA LEAF; CLOVE; FUCUS VESICULOSUS; COPPER GLUCONATE; PHENOXYETHANOL; SALICORNIA EUROPAEA WHOLE; CALCIUM GLUCONATE; UNDARIA PINNATIFIDA; GINGER; SODIUM CARBONATE

Mara Clear Skin Mineral Milk Acne Treatment

Active Ingredients

Salicylic Acid 2%

Purpose

Acne Treatment

Uses

- For the treatment of acne.
- Penetrates pores to eliminate most acne blemishes, blackheads and whiteheads.
- Helps prevent new acne blemishes, blackheads and whiteheads.

Warnings

- For external use only.

When using this product

- skin irritation and dryness is more likely to occur if you use another topical acne medication at the same time. If irritation occurs, only use one topical acne medication at a time.

Directions

- Clean the skin thoroughly before applying this product.
- Cover the entire affected area with a thin layer one time daily.
- Because excessive drying of the skin may occur, start with one application daily, then gradually increase to two or three times daily if needed or as directed by a doctor.
- If bothersome dryness or peeling occurs, reduce application to once a day or every other day.

Inactive Ingredients

AQUA (WATER), SIMMONDSIA CHINENSIS (JOJOBA) SEED OIL, C13-15 ALKANE, VITIS VINIFERA (GRAPE) SEED OIL, GLYCERIN, POLYGLYCERYL 3 POLYRICINOLEATE, CAPRYLIC/CAPRIC TRIGLYCERIDE, NIACINAMIDE, DISTEARDIMONIUM HECTORITE, NIGELLA SATIVA SEED OIL, BAKUCHIOL, CUCURBITA PEPO (PUMPKIN) SEED OIL, CORYLUS AVELLANA (HAZELNUT) SEED OIL, CALOPHYLLUM INOPHYLLUM SEED OIL, SODIUM CHLORIDE, GLUCONOLACTONE, MAGNESIUM PCA, MANDELIC ACID, SODIUM BENZOATE, BISABOLOL, HELIANTHUS ANNUUS (SUNFLOWER) SEED OIL, LAMINARIA HYPERBOREA EXTRACT, ZINC PCA, SODIUM HYDROXIDE, MAGNESIUM ASPARTATE, ZINC GLUCONATE, CRAMBE MARITIMA LEAF EXTRACT, EUGENIA CARYOPHYLLUS (CLOVE) BUD EXTRACT, FUCUS VESICULOSUS EXTRACT, COPPER GLUCONATE, PHENOXYETHANOL, SALICORNIA HERBACEA EXTRACT, CALCIUM GLUCONATE, UNDARIA PINNATIFIDA EXTRACT, ZINGIBER OFFICINALE (GINGER) ROOT EXTRACT, SODIUM CARBONATE

Questions or Comments?

310-984-4504